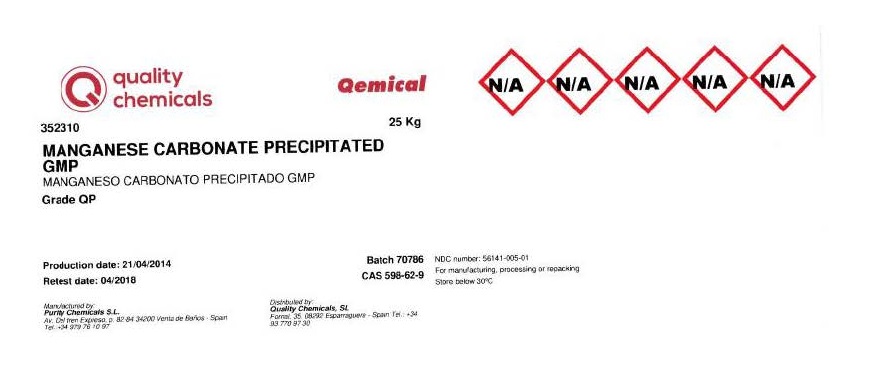 DRUG LABEL: Manganese carbonate
NDC: 56141-002 | Form: POWDER
Manufacturer: Quality Chemicals S.L.
Category: other | Type: BULK INGREDIENT - ANIMAL DRUG
Date: 20211129

ACTIVE INGREDIENTS: MANGANESE CARBONATE 1 kg/1 kg

Manganese carbonate